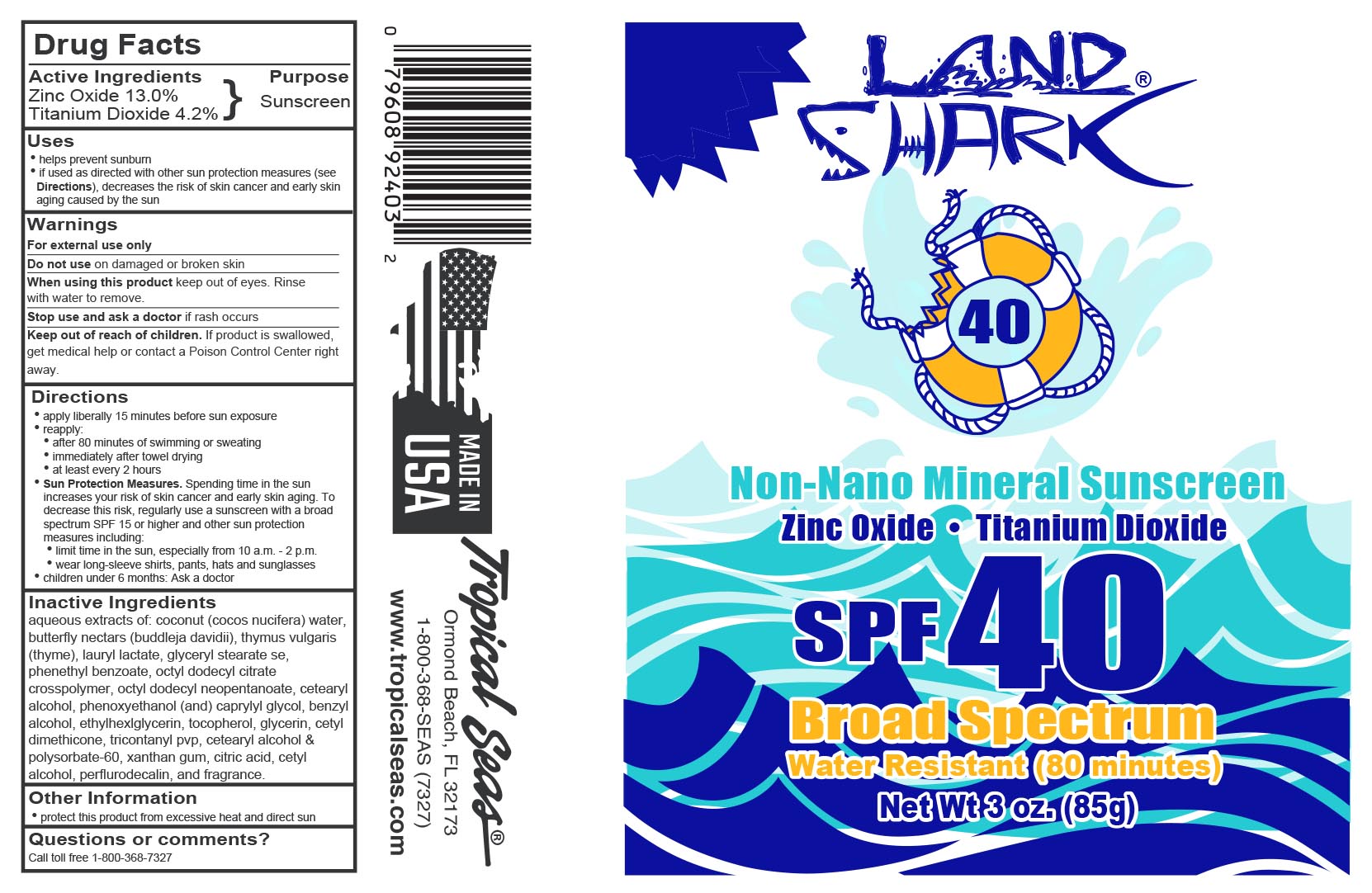 DRUG LABEL: Land Shark SPF 40
NDC: 52854-403 | Form: LOTION
Manufacturer: Tropical Seas, Inc.
Category: otc | Type: HUMAN OTC DRUG LABEL
Date: 20251104

ACTIVE INGREDIENTS: ZINC OXIDE 13 g/100 g; TITANIUM DIOXIDE 4.2 g/100 g
INACTIVE INGREDIENTS: CETYL ALCOHOL; TRIACONTANYL PVP (WP-660); CITRIC ACID MONOHYDRATE; ETHYLHEXYLGLYCERIN; THYMUS VULGARIS LEAF; BENZYL ALCOHOL; TOCOPHEROL; LAURYL LACTATE; COCONUT WATER; CETOSTEARYL ALCOHOL; CETYL DIMETHICONE 150; GLYCERYL STEARATE SE; WATER; BUDDLEJA DAVIDII LEAF; GLYCERIN; OCTYLDODECYL NEOPENTANOATE; PERFLUOROMETHYLDECALIN; PHENOXYETHANOL; CAPRYLYL GLYCOL; POLYSORBATE 60; XANTHAN GUM; PHENETHYL BENZOATE; OCTYLDODECYL CITRATE CROSSPOLYMER

Land Shark SPF 40 Non-Nano Mineral Sunscreen

Drug Facts

Active Ingredients

Zinc Oxide 13.0%

Titanium Dioxide 4.2%

Purpose

Sunscreen

Uses

- helps prevent sunburn
- if used as directed with other sun protection measures (see Directions), decreases the risk of skin cancer and early skin aging caused by the sun

Warnings

For external use only

Do not use on damaged or broken skin

When using this product keep out of eyes. Rinse with water to remove.

Stop use and ask a doctor if rash occurs

Keep out of reach of children. If product is swallowed, get medical help or contact a Poison Control Center right away.

Directions

- apply liberally 15 minutes before sun exposure
- reapply:
  - after 80 minutes of swimming or sweating
  - immediately after towel drying
  - at least every 2 hours
- Sun Protection Measures. Spending time in the sun increases your risk of skin cancer and early skin aging. To decrease this risk, regularly use a sunscreen with a broad spectrum SPF 15 or higher and other sun protection measures including:
  - limit time in the sun, especially from 10 a.m. - 2 p.m.
  - wear long-sleeve shirts, pants, hats and sunglasses
- children under 6 months: Ask a doctor

Inactive Ingredients

aqueous extracts of: coconut (cocos nucifera) water, butterfly nectars (buddleja davidii), thymus vulgaris (thyme), lauryl lactate, glyceryl stearate se, phenethyl benzoate, octyl dodecyl citrate crosspolymer, octyl dodecly neopentanoate, cetearyl alcohol, phenoxyethanol (and) caprylyl glycol, benzyl alcohol, ethylhexlglycerin, tocopherol, glycerin, cetyl dimethicone, tricontanyl pvp, cetearyl alcohol & polysorbate-60, xanthan gum, citric acid, cetyl alcohol, perflurodecalin, and fragrance.

Other Information

- protect this product from excessive heat and direct sun

Questions or comments?

Call toll free 1-800-368-7327

Principal Display Panel - 85 g Tube Art

85g NDC 52854-403-01